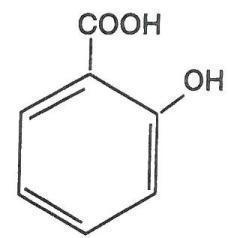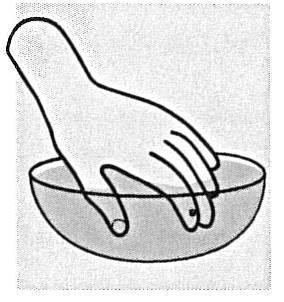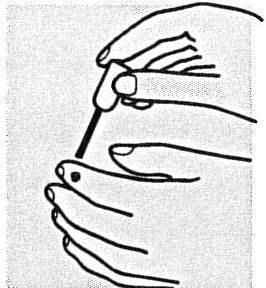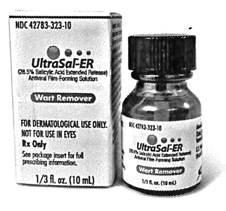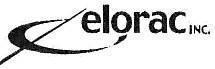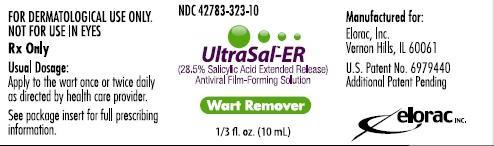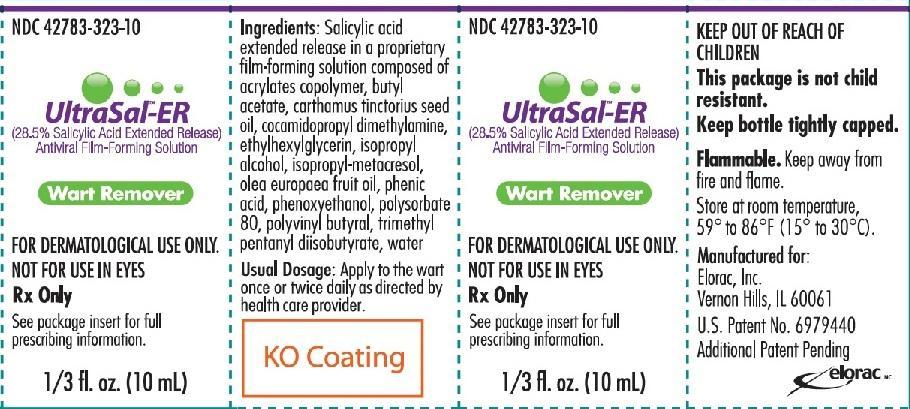 DRUG LABEL: Ultrasal-ER
NDC: 42783-323 | Form: SOLUTION
Manufacturer: Elorac, Inc.
Category: prescription | Type: HUMAN PRESCRIPTION DRUG LABEL
Date: 20211208

ACTIVE INGREDIENTS: salicylic acid 285 mg/1 mL

Ultrasal-ER (28.5% Salicylic Acid Extended Release) Antiviral Film-Forming Solution: Package Insert

Rx only

FOR TOPICAL USE ONLY.

NOT FOR OPHTHALMIC, ORAL OR INTRAVAGINAL USE.

DESCRIPTION

UltraSal-ER is a topical preparation containing 28.5% salicylic acid extended release in a proprietary film-forming virucidal solution composed of acrylates copolymer, butyl acetate, carthamus tinctorius seed oil, cocamidopropyl dimethylamine, ethylhexylglycerin, isopropyl alcohol, isopropyl-metacresol, olea europaea fruit oil, phenic acid, phenoxyethanol, polysorbate 80, polyvinyl butyral, trimethyl pentanyl diisobutyrate, and water. The pharmacologic activity of UltraSal-ER is generally attributed to the keratolytic activity of salicylic acid, which is incorporated into a polyacrylic, film-forming virucidal solution designed to cover the wart without the need for a bandage. The structural formula of salicylic acid is:

CLINICAL PHARMACOLOGY

Although the exact mode of action for salicylic acid in the treatment of warts is unknown, its activity appears to be associated with its keratolytic action, which results in mechanical removal of epidermal cells infected with wart viruses. UltraSal-ER incorporates a unique patented extended release form of salicylic acid that provides for enhanced release of salicylic acid for over 24 hours.

The virucidal complex incorporated into UltraSal-ER’s proprietary solution is designed to help reduce risk of reinfection at the wart site, as well as prevent viral contamination of the product under normal usage.

INDICATIONS AND USAGE

UltraSal-ER is indicated for the topical treatment and removal of common warts and plantar warts.

CONTRAINDICATIONS

Patients with diabetes or impaired blood circulation should not use UltraSal-ER. UltraSal-ER also should not be used on moles, birthmarks, and unusual warts with hair growing from them, or warts on the face.

PRECAUTIONS

UltraSal-ER is for external use only. Do not permit UltraSal-ER to contact eyes or mucous membranes. If contact with eyes or mucous membranes occurs, immediately flush with water for 15 minutes. UltraSal-ER should not be allowed to contact normal skin surrounding the wart site, since localized irritation may occur. Treatment should be discontinued if excessive irritation occurs.

UltraSal-ER is flammable. Keep away from fire or flame. Keep bottle tightly capped when not in use.

ADVERSE REACTIONS

A localized irritant reaction may occur if Ultrasal-ER is applied to the normal skin surrounding the wart. Any irritation may normally be controlled by temporarily discontinuing use and by applying the medication only to the wart site when treatment is resumed.

DOSAGE AND ADMINISTRATION

Prior to applying UltraSal-ER, soak wart in warm water for five minutes. Remove any loose tissue by gently rubbing with a washcloth, emery board, or pumice stone. Dry the wart site thoroughly. Using the brush applicator supplied, apply UltraSal-ER twice to the entire wart surface, allowing the first application to dry before applying the second. Continue treatment once or twice a day as directed by your healthcare provider. Be careful not to apply to surrounding skin.

Clinically visible improvement normally occurs during the first or second week of therapy. Resolution may be expected after four to six weeks of UltraSal-ER use, though some warts may take longer to remove.

HOW SUPPLIED

UltraSal-ER is supplied in 10 mL amber bottles with a brush applicator (NDC 42783-323-10).

Store at 15° to 30°C (59° to 86°F).

Manufactured for:

Elorac, Inc.

Vernon Hills, IL 60061

U.S. Patent No. 6,979,440

Additional Patent Pending

© 2014 Elorac, Inc.

1/2014

211909

PATIENT INSTRUCTIONS

Your health care provider has prescribed UltraSal-ER, a topical prescription preparation for the treatment of common warts and plantar warts. In order for UltraSal-ER to work properly and to ensure maximum benefit, the following instructions should be followed carefully. Of course, as with any medication, always consult your health care provider if you experience any discomfort or unexpected reactions.

STEP 1

WASH

- Soak wart area in warm water for about 5 minutes.
- Remove any loose tissue using a washcloth, emery board, or pumice stone.
- Dry thoroughly.

STEP 2

BRUSH

- Using the brush applicator supplied, apply twice to entire wart surface, allowing the first application to dry before applying the second.
- Be careful not to apply to surrounding skin.
- Leave UltraSal-ER on wart area after it dries.

Repeat Step 1 and Step 2 once or twice daily as advised by the health care provider.

Clinically visible improvement will normally occur during the first or second week of therapy. Resolution may be expected after four to six weeks of UltraSal-ER use, though some warts may take longer to remove.

Vernon Hills, IL 60061

Ultrasal-ER (28.5% Salicylic Acid Extended Release) Antiviral Film-Forming Solution: Container Label Principal Display Panel

NDC 42783-323-10

Ultrasal-ER (28.5% Salicylic Acid Extended Release) Antiviral Film-Forming Solution

1/3 fl. oz. (10 mL)

Rx only

Ultrasal-ER (28.5% Salicylic Acid Extended Release) Antiviral Film-Forming Solution: Carton Label Principal Display Panel

NDC 42783-323-10

Ultrasal-ER (28.5% Salicylic Acid Extended Release) Antiviral Film-Forming Solution

1/3 fl. oz. (10 mL)

Rx only